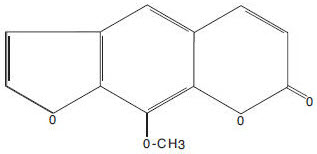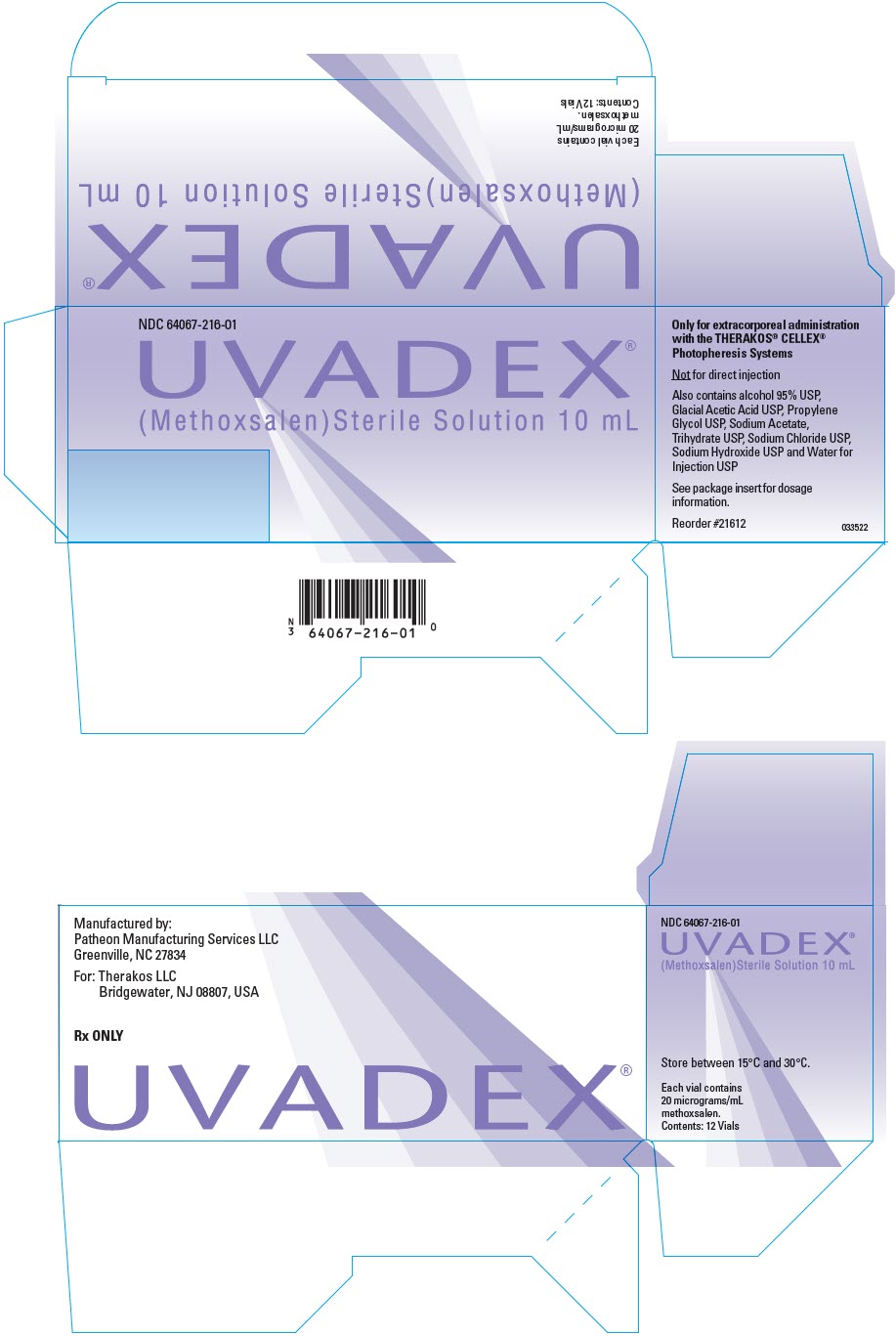 DRUG LABEL: UVADEX
NDC: 64067-216 | Form: INJECTION, SOLUTION
Manufacturer: Therakos LLC
Category: prescription | Type: HUMAN PRESCRIPTION DRUG LABEL
Date: 20241216

ACTIVE INGREDIENTS: METHOXSALEN 20 ug/1 mL

UVADEX®
(Methoxsalen)
STERILE SOLUTION, 20 mcg/mL

Rx ONLY.

CAUTION: READ THE THERAKOS® CELLEX® PHOTOPHERESIS SYSTEM OPERATOR'S MANUAL PRIOR TO PRESCRIBING OR DISPENSING THIS MEDICATION.

BOXED WARNING

UVADEX® (methoxsalen) Sterile Solution should be used only by physicians who have special competence in the diagnosis and treatment of cutaneous T-cell lymphoma and who have special training and experience in the THERAKOS® CELLEX® Photopheresis System. Please consult the CELLEX® Operator's Manual before using this product.

DESCRIPTION

Methoxsalen is a naturally occurring photoactive substance found in the seeds of the Ammi majus (Umbelliferae) plant. It belongs to a group of compounds known as psoralens or furocoumarins. The chemical name of methoxsalen is 9-methoxy-7H-furo[3,2-g][1]-benzopyran-7-one; it has the following structure:

Each mL of UVADEX® (methoxsalen, 8-methoxypsoralen) Sterile Solution contains methoxsalen 20 mcg, propylene glycol 50 mg, sodium chloride 8 mg, sodium acetate 1.75 mg, ethanol 40.550 mg, glacial acetic acid 1.260 mg, and Water for Injection q.s. to 1.0 mL. Glacial acetic acid and sodium hydroxide are used to adjust the pH of the solution if necessary. UVADEX® is a clear, colorless to pale yellow liquid.

UVADEX® is used in combination with the THERAKOS® CELLEX® Photopheresis System to extracorporeally treat leukocyte enriched buffy coat.

CLINICAL PHARMACOLOGY

Mechanism of action

The exact mechanism of action of methoxsalen is not known. The best-known biochemical reaction of methoxsalen is with DNA. Methoxsalen, upon photoactivation, conjugates and forms covalent bonds with DNA which leads to the formation of both monofunctional (addition to a single strand of DNA) and bifunctional adducts (crosslinking of psoralen to both strands of DNA). Reactions with proteins have also been described. The formation of photoadducts results in inhibition of DNA synthesis, cell division and epidermal turnover.

For the palliative treatment of Cutaneous T-Cell Lymphoma, Photopheresis consists of removing a portion of the patient's blood and separating the red blood cells from the white cell layer (buffy coat) by centrifugation. The red cells are returned to the patient and the UVADEX® Sterile Solution is then injected into the instrument and mixed with the buffy coat. The instrument then irradiates this drug-cell mixture with ultraviolet light (UVA light, 320–400 nm) and returns the treated cells to the patient. See the appropriate Operator's Manual for details of this process. Although extracorporeal phototherapy exposes less than 10% of the total body burden of malignant cells to methoxsalen plus light, some patients achieve a complete response. Animal studies suggest that the photopheresis may activate an immune-mediated response against the malignant T-cells.

Use of the THERAKOS® UVAR and UVAR XTS® Photopheresis Systems after oral administration of methoxsalen were previously approved for the treatment of Cutaneous T-Cell Lymphoma. Interpatient variability in peak plasma concentration after an oral dose of methoxsalen ranges from 6 to 15 fold. UVADEX® is injected directly into the separated buffy coat in the instrument in an attempt to diminish this interpatient variability and to improve the exposure of the cells to the drug.

Methoxsalen is reversibly bound to serum albumin and is also preferentially taken up by epidermal cells. Methoxsalen is rapidly metabolized in humans, with approximately 95% of the drug excreted as metabolites in the urine within 24 hours.

Systemic administration of methoxsalen followed by UVA exposure leads to cell injury. The most obvious manifestation of this injury after skin exposure is delayed erythema, which may not begin for several hours and peaks at 48–72 hours. The inflammation is followed over several days to weeks, by repair which is manifested by increased melanization of the epidermis and thickening of the stratum corneum.

The total dose of methoxsalen delivered in UVADEX® is substantially lower (approximately 200 times) than that used with oral administration. More than 80% of blood samples collected 30 minutes after reinfusion of the photoactivated buffy coat had methoxsalen levels below detection limits of the assay (<10 ng/ml), and the mean plasma methoxsalen concentration was approximately 25 ng/ml.

CLINICAL STUDIES

Three single-arm studies were performed to evaluate the effectiveness of photopheresis in the treatment of the skin manifestations of Cutaneous T-Cell Lymphoma (CTCL). In the first study (CTCL 1), 39 patients were treated with the oral formulation of methoxsalen in conjunction with the UVAR Photopheresis System. The second study (CTCL 2) was a 5-year post approval follow-up of 57 CTCL patients that was conducted to evaluate long-term safety. This study also used the oral dosage formulation of methoxsalen. In the third study (CTCL 3), 51 patients were treated with the UVADEX® formulation of methoxsalen in conjunction with the UVAR Photopheresis System. In study CTCL 3, 86% of the patients were Caucasian, the median age was 62 years, and the average number of prior therapies was 4.3.

In study CTCL 1, prednisone up to 10 mg/day was permitted in addition to topical steroids. In CTCL 2, there was no concomitant medication restriction. In CTCL 3, topical steroids were permitted only for the treatment of fissures on the soles of the feet and the palms of hands. All other steroids, topical or systemic, were prohibited.

In all three studies, patients were initially treated on two consecutive days every four to five weeks. If the patient did not respond after four cycles, treatment was accelerated to two consecutive days every other week. If the patient did not respond after four cycles at the accelerated schedule, the patient was treated on two consecutive days every week. If the patient still did not respond after four cycles of weekly treatments, the schedule was increased to three consecutive days every week for three cycles. In study CTCL 3, 15 of the 17 responses were seen within six months of treatment. Only two patients responded to treatment after six months. Clinical experience does not extend beyond this treatment frequency and there is no evidence to show that treatment with UVADEX® beyond six months or using a different schedule provided additional benefit.

Overall skin scores were used in the clinical studies of photopheresis to assess the patient's response to treatment. The patient's baseline skin score was used for comparison with subsequent scores. A 25% reduction in skin score maintained for four consecutive weeks was considered a successful response to photopheresis therapy. Table 1 indicates the percent of successful responses within six months of beginning therapy for all patients who received at least one course of photopheresis. Only patients with patch plaque, extensive plaque and erythrodermic disease were enrolled in these studies. No patients with disease in the tumor phase were treated. There are no data available regarding the efficacy of UVADEX® in patients with disease in the tumor phase.

Table 1: Percentage of Successful Responses Within Six Months of Beginning Therapy
Study | Response % Within Six Months
CTCL 3 (UVADEX®) | 17/51 (33)
CTCL 2 (oral methoxsalen) | 16/57 (28)
CTCL 1 (oral methoxsalen) | 21/39 (54)

Although the response rate with UVADEX® in CTCL 3 was similar to with oral methoxsalen in CTCL 2, the possibility that UVADEX® is inferior in efficacy to oral methoxsalen cannot be excluded due to the design and size of the clinical trials. The higher response rate with oral methoxsalen in CTCL 1 may be partly due to patients receiving more treatments (mean of 64 in CTCL 1, 31 in CTCL 2, and 20 in CTCL 3), and to the administration of systemic steroids in CTCL 1.

Retrospective analyses of three clinical benefit parameters from the Body Area Severity Scores in CTCL 3 suggested a correlation between skin score response and improvement in edema, scaling and resolution of fissures.

INDICATIONS AND USAGE

UVADEX® (methoxsalen) Sterile Solution is indicated for extracorporeal administration with the THERAKOS® CELLEX® Photopheresis System in the palliative treatment of the skin manifestations of Cutaneous T-Cell Lymphoma (CTCL) that is unresponsive to other forms of treatment.

CONTRAINDICATIONS

- UVADEX® (methoxsalen) Sterile Solution is contraindicated in patients exhibiting idiosyncratic or hypersensitivity reactions to methoxsalen, other psoralen compounds or any of the excipients. Patients possessing a specific history of a light sensitive disease state should not initiate methoxsalen therapy. Diseases associated with photosensitivity include lupus erythematosus, porphyria cutanea tarda, erythropoietic protoporphyria, variegate porphyria, xeroderma pigmentosum and albinism.
- UVADEX® Sterile Solution is contraindicated in patients with aphakia, because of the significantly increased risk of retinal damage due to the absence of lenses.
- Patients should not receive UVADEX® if they have any contraindications to the photopheresis procedure.

WARNINGS

Concomitant Therapy

Patients who are receiving concomitant therapy (either topically or systemically) with known photosensitizing agents such as anthralin, coal tar or coal tar derivatives, griseofulvin, phenothiazines, nalidixic acid, halogenated salicylanilides (bacteriostatic soaps), sulfonamides, tetracyclines, thiazides, and certain organic staining dyes such as methylene blue, toluidine blue, rose bengal and methyl orange may be at greater risk for photosensitivity reactions with UVADEX®.

Carcinogenicity, Mutagenesis, Impairment of Fertility

Oral administration of methoxsalen followed by cutaneous UVA exposure (PUVA therapy) is carcinogenic. In a prospective study of 1380 patients given PUVA therapy for psoriasis, 237 patients developed 1422 cutaneous squamous cell cancers. This observed incidence of cutaneous carcinoma is 17.6 times that expected for the general population. Previous cutaneous exposure to tar and UVB treatment, ionizing radiation or arsenic increased the risk of developing skin carcinomas after PUVA therapy. Because the dose of methoxsalen with UVADEX® therapy is about 200 times less than with PUVA and the skin is not exposed to high cumulative doses of UVA light, the risk of developing skin cancer following UVADEX® therapy may be lower.

Methoxsalen was carcinogenic in male rats that were given the drug by oral gavage five days per week for 103 weeks at doses of 37.5 and 75 mg/kg. The 37.5 mg/kg dose is about 1900 times greater than a single human methoxsalen dose during extracorporeal photopheresis treatment on a body surface area basis. The neoplastic lesions in rats included adenomas and adenocarcinomas of the tubular epithelium of the kidneys, carcinoma or squamous cell carcinoma of the Zymbal gland and alveolar or bronchiolar adenomas. Topical or intraperitoneal methoxsalen is a potent photo-carcinogen in albino mice and hairless mice.

With S9 activation, methoxsalen is mutagenic in the Ames test. In the absence of S9 activation and UV light, methoxsalen is clastogenic in vitro (sister chromatid exchange and chromosome aberrations in Chinese hamster ovary cells). Methoxsalen also causes DNA damage, interstrand cross-links and errors in DNA repair.

Pregnancy

Methoxsalen may cause fetal harm when given to a pregnant woman. Doses of 80 to 160 mg/kg/day given during organogenesis caused significant fetal toxicity in rats. The lowest of these doses, 80 mg/kg/day, is over 4000 times greater than a single dose of UVADEX® on a mg/m^2 basis. Fetal toxicity was associated with significant maternal weight loss, anorexia and increased relative liver weight. Signs of fetal toxicity included increased fetal mortality, increased resorptions, late fetal death, fewer fetuses per litter, and decreased fetal weight. Methoxsalen caused an increase in skeletal malformation and variations at doses of 80 mg/kg/day and above. There are no adequate and well-controlled studies of methoxsalen in pregnant women. If UVADEX® is used during pregnancy, or if the patient becomes pregnant while receiving UVADEX®, the patient should be apprised of the potential hazard to the fetus. Women of childbearing potential should be advised to avoid becoming pregnant.

Photosensitivity

Severe photosensitivity can occur in patients treated with UVADEX®. Advise patients to wear UVA absorbing, wrap-around sunglasses and cover exposed skin or use a sunblock (SP 15 or higher), and avoid all exposure to sunlight for twenty-four (24) hours following photopheresis treatment. See Precautions section for additional information.

PRECAUTIONS

General

ACTINIC DEGENERATION

After methoxsalen administration, exposure to sunlight and/or ultraviolet radiation may result in "premature aging" of the skin.

BASAL CELL CARCINOMAS

Since oral psoralens may increase the risk of skin cancers, monitor closely those patients who exhibit multiple basal cell carcinomas or who have a history of basal cell carcinomas.

SERIOUS SKIN BURNS

Serious burns from either UVA or sunlight (even through window glass) can result if the recommended dosage of methoxsalen is exceeded or precautions are not followed. Advise patients to avoid all exposure to sunlight during the 24 hours following photopheresis treatment.

CATARACT FORMATION

Exposure to large doses of UVA light causes cataracts in animals. Oral methoxsalen exacerbates this toxicity. The concentration of methoxsalen in the human lens is proportional to the concentration in serum. Serum methoxsalen concentrations are substantially lower after extracorporeal UVADEX® treatment than after oral methoxsalen treatment. Nevertheless, if the lens is exposed to UVA light while methoxsalen is present, photoactivation of the drug may cause adducts to bind to biomolecules within the lens. If the lens is shielded from UVA light, the methoxsalen will diffuse out of the lens in about 24 hours.

Patients who use proper eye protection after PUVA therapy (oral methoxsalen) appear to have no increased risk of developing cataracts. The incidence of cataracts in these patients five years after their first treatment is about the same as that in the general population.

Instruct patients emphatically to wear UVA absorbing, wrap-around sunglasses for twenty-four (24) hours after UVADEX® treatment. They should wear these glasses any time they are exposed to direct or indirect sunlight, whether they are outdoors or exposed through a window.

VENOUS AND ARTERIAL THROMBOEMBOLISM

Thromboembolic events, such as pulmonary embolism and deep vein thrombosis, have been reported with UVADEX® administration through photopheresis systems for treatment of patients with graft-versus-host disease, a disease for which UVADEX® is not approved.

Information for Patients

Patients should be told emphatically to wear UVA-absorbing, wrap-around sunglasses and cover exposed skin or use a sunblock (SP 15 or higher) for the twenty-four (24) hour period following treatment with methoxsalen, whether exposed to direct or indirect sunlight in the open or through a window glass.

Drug Interactions

See Warnings Section.

Carcinogenesis, Mutagenesis, and Impairment of Fertility

See Warnings Section.

Nursing Mothers

It is not known whether this drug is excreted in human milk. Because many drugs are excreted in human milk, caution should be exercised when methoxsalen is administered to a nursing woman.

Pediatric Use

Safety in children has not been established. Potential hazards of long-term therapy include the possibilities of carcinogenicity and cataractogenicity as described in the Warnings Section as well as the probability of actinic degeneration which is also described in the Warnings Section.

Patients with Renal or Hepatic Impairment

UVADEX® has not been evaluated in patients with renal or hepatic impairment

Renal impairment

Although renal transplant recipients with poor renal function have been treated with photopheresis using UVADEX®, little additional information is available on the use of UVADEX® in patients with varying degree of renal impairment. No reduction of dose or prolongation of UV light protection were reported in the renal transplant recipients who have undergone photopheresis treatment.

Hepatic impairment

No specific information is available on the use of photopheresis with UVADEX® in patients with hepatic impairment. In view of the very low systemic exposure to methoxsalen, it is unlikely that patients with severe hepatic impairment will be at greater risk than patients with normal hepatic function. However, the potential benefits of photopheresis treatment should be weighed against any possible risk before embarking on the procedure.

ADVERSE REACTIONS

Side effects of photopheresis (UVADEX® used with THERAKOS® Photopheresis Systems) were primarily related to hypotension secondary to changes in extracorporeal volume (>1%). In study CTCL 3 (UVADEX®), six serious cardiovascular adverse experiences were reported in five patients (5/51, 10%). Five of these six events were not related to photopheresis and did not interfere with the scheduled photopheresis treatments. One patient (1/51, 2%) with ischemic heart disease had an arrhythmia after the first day of photopheresis that was resolved the next day. Six infections were also reported in five patients. Two of the six events were Hickman catheter infections in one patient, which did not interrupt the scheduled photopheresis. The other four infections were not related to photopheresis and did not interfere with scheduled treatments.

POSTMARKETING

Adverse reactions reported from postmarketing experience include nausea, dysgeusia, photosensitivity reaction, pyrexia and hypersensitivity reactions including anaphylaxis and rash.

OVERDOSAGE

In the event of overdosage, the patient should be kept in a darkened room for at least 24 hours.

DRUG DOSAGE AND ADMINISTRATION

Each UVADEX® treatment involves collection of leukocytes, photoactivation, and reinfusion of photoactivated cells. UVADEX® (methoxsalen) Sterile Solution is supplied in 10 mL vials containing 200 mcg of methoxsalen (concentration of 20 mcg/mL). The THERAKOS® CELLEX® Photopheresis System Operator's Manual should be consulted before using this product. UVADEX® should not be diluted. The contents of the vial should be injected into the THERAKOS® CELLEX® Photopheresis System immediately after being drawn up into a syringe. Do not inject directly into patients. The UVADEX® vial is for single use only. Any UVADEX® that is not used during a procedure should be immediately discarded. UVADEX® can adsorb onto PVC and plastics, therefore only THERAKOS® CELLEX® photopheresis procedural kits supplied for use with the instrument should be used to administer this medicinal product. Once UVADEX® is drawn into a plastic syringe it should be immediately injected into the photoactivation bag. UVADEX® exposed to a plastic syringe for more than one hour should be discarded.

During treatment with the THERAKOS® CELLEX® Photopheresis System, the dosage of UVADEX® for each treatment will be calculated according to the treatment volume.

- The prescribed amount of UVADEX® should be injected into the recirculation bag prior to the Photoactivation Phase using the formula:

TREATMENT VOLUME × 0.017 = mL of UVADEX® for each treatment

Example: Treatment volume of 240 mL × 0.017 = 4.1 mL of UVADEX®

Frequency/Schedule of Treatment

Normal Treatment Schedule

Treatment is given on two consecutive days every four weeks for a minimum of seven treatment cycles (six months).

Accelerated Treatment Schedule

If the assessment of the patient during the fourth treatment cycle (approximately three months) reveals an increased skin score from the baseline score, the frequency of treatment may be increased to two consecutive treatments every two weeks. If a 25% improvement in the skin score is attained after four consecutive weeks, the regular treatment schedule may resume. Patients who are maintained in the accelerated treatment schedule may receive a maximum of 20 cycles. There is no clinical evidence to show that treatment with UVADEX® beyond six months or using a different schedule provides additional benefit. In study CTCL 3, 15 of the 17 responses were seen within six months of treatment and only two patients responded to treatment after six months.

HOW SUPPLIED

STORAGE AND HANDLING

UVADEX® (methoxsalen) Sterile Solution 20 mcg/mL in 10 mL amber glass vials (NDC 64067-216-01), and cartons of 12 vials (NDC 64067-216-01). One vial of 10 mL contains 200 micrograms methoxsalen. The drug product must be stored between 59°F (15°C) and 86°F (30°C)

REFERENCES

1. Recommendations for the Safe Handling of Parenteral Antineoplastic Drugs, NIH Publication No. 83-2621. For sale by the Superintendent of Documents, U.S. Government Printing Office, Washington, DC 20402.
2. AMA Council Report, Guidelines for Handling of Parenteral Antineoplastics. JAMA, 1985; 2.53 (11): 1590–1592.
3. National Study Commission on Cytotoxic Exposure- Recommendations for Handling Cytotoxic Agents. Available from Louis P. Jeffrey, ScD., Chairman, National Study Commission on Cytotoxic Exposure, Massachusetts College of Pharmacy and Allied Health Sciences, 179 Longwood Avenue, Boston, Massachusetts 02115.
4. Clinical Oncological Society of Australia, Guidelines and Recommendations for Safe Handling of Antineoplastic Agents. Med J Australia, 1983; 1:426–428.
5. Jones, RB, et al. Safe Handling of Chemotherapeutic Agents: A Report from The Mount Sinai Medical Center. CA- A Cancer Journal for Clinicians, 1983;(Sept/Oct) 258–263.
6. American Society of Hospital Pharmacists Technical Assistance Bulletin of Handling Cytotoxic and Hazardous Drugs. Am J. Hosp Pharm, 1990;47:1033–1049.
7. Controlling Occupational Exposure to Hazardous Drugs. (OSHA Work-Practice Guidelines), AM J. Health-Syst Pharm, 1996; 53: 1669–1685.

Manufactured by Patheon Manufacturing Services LLC, Greenville, NC 27834
For Therakos LLC, Bridgewater, NJ 08807, USA

November 2024
NDA 20-969

PRINCIPAL DISPLAY PANEL - 10 mL Vial Carton

NDC 64067-216-01

UVADEX®
(Methoxsalen) Sterile Solution 10 mL